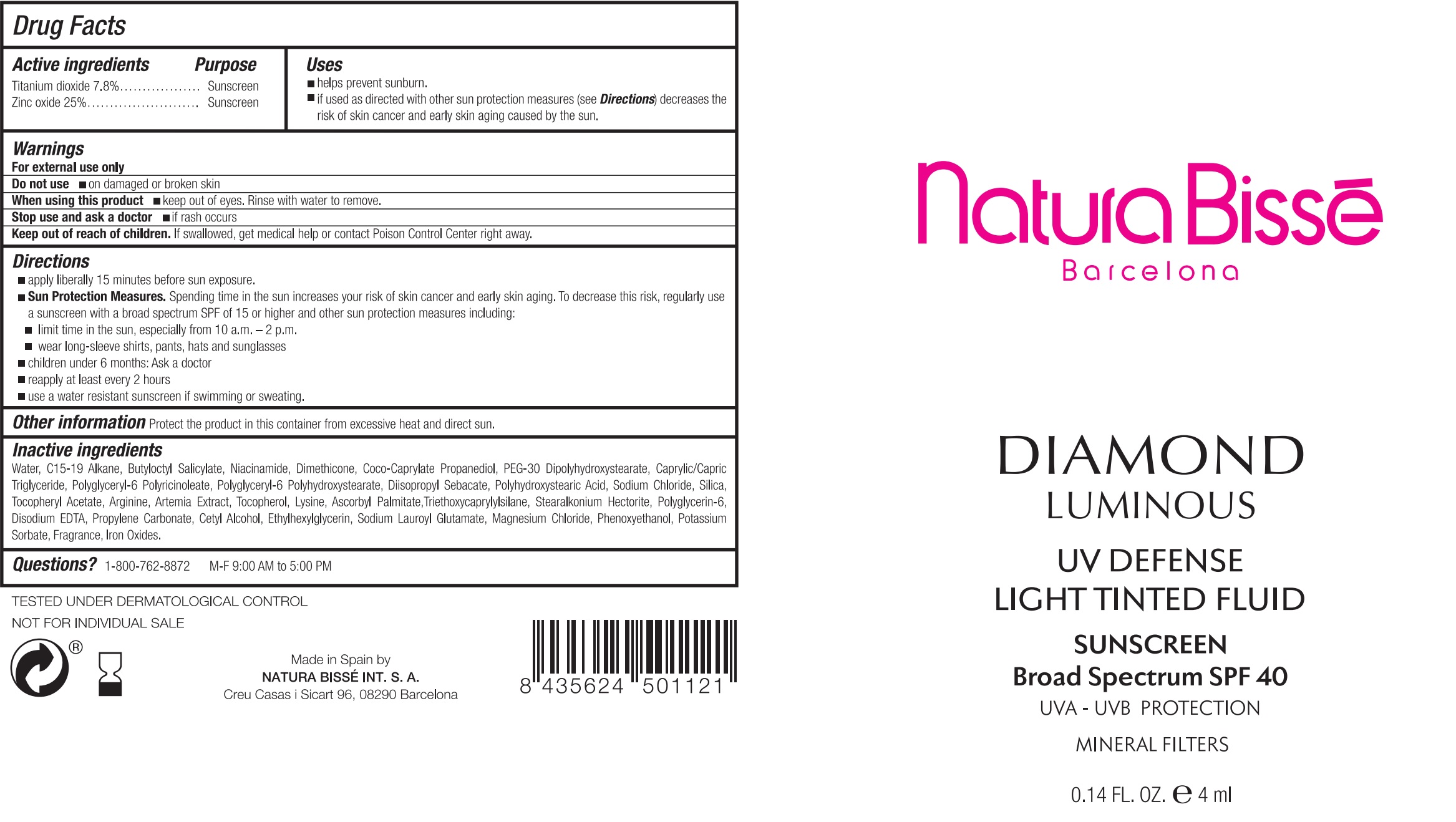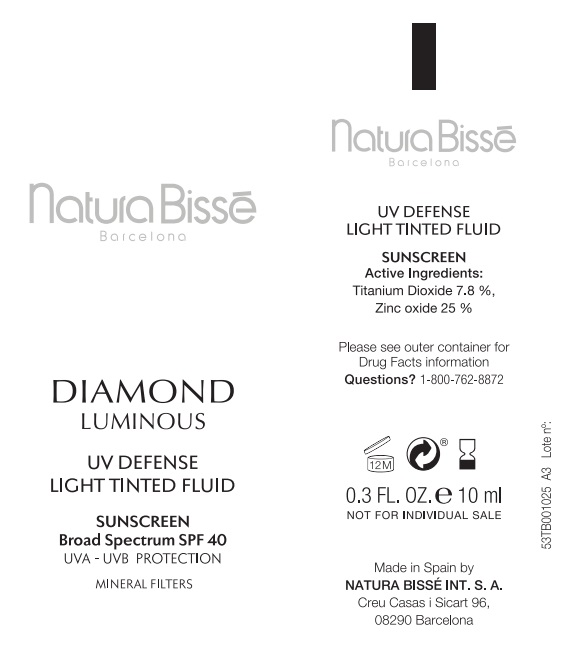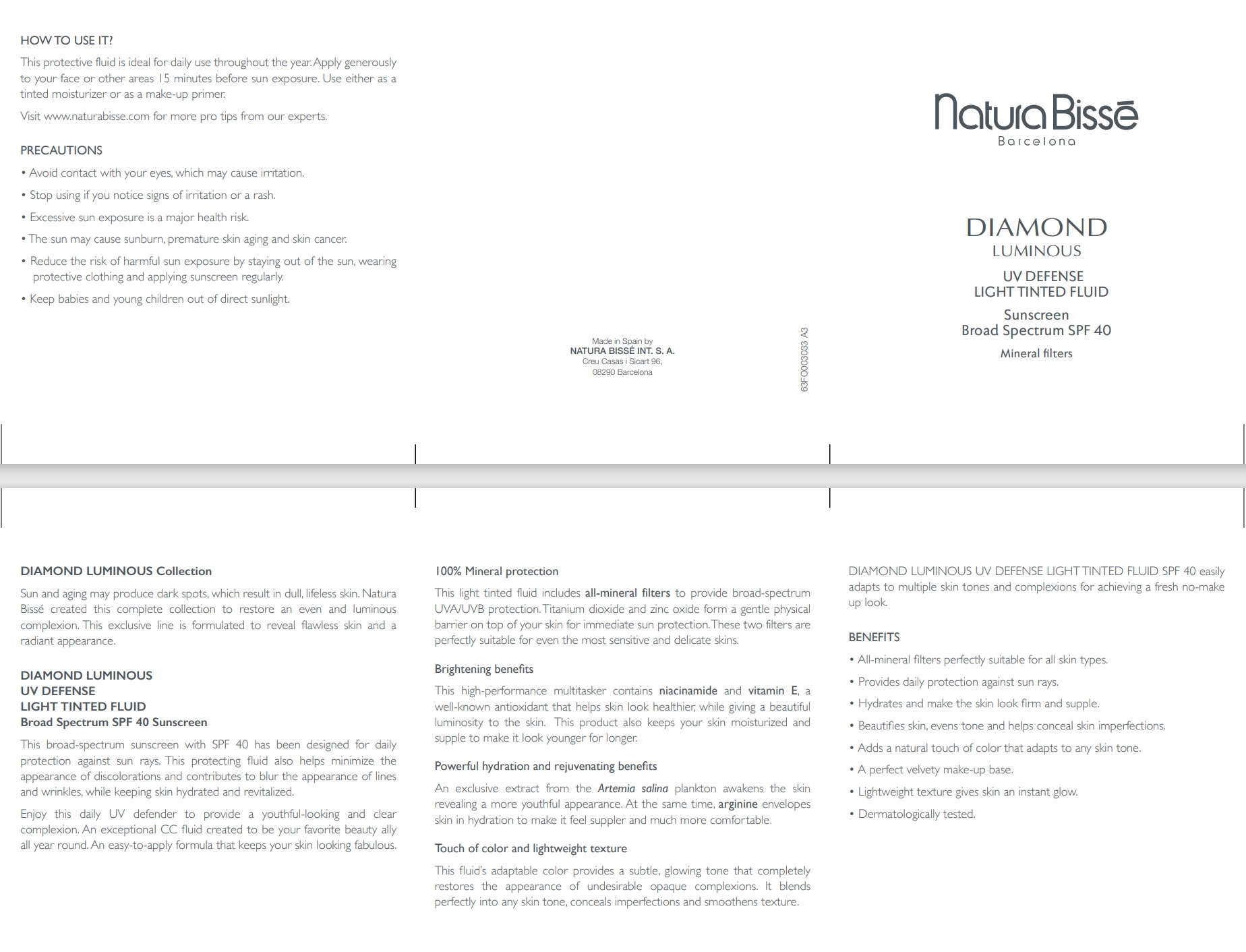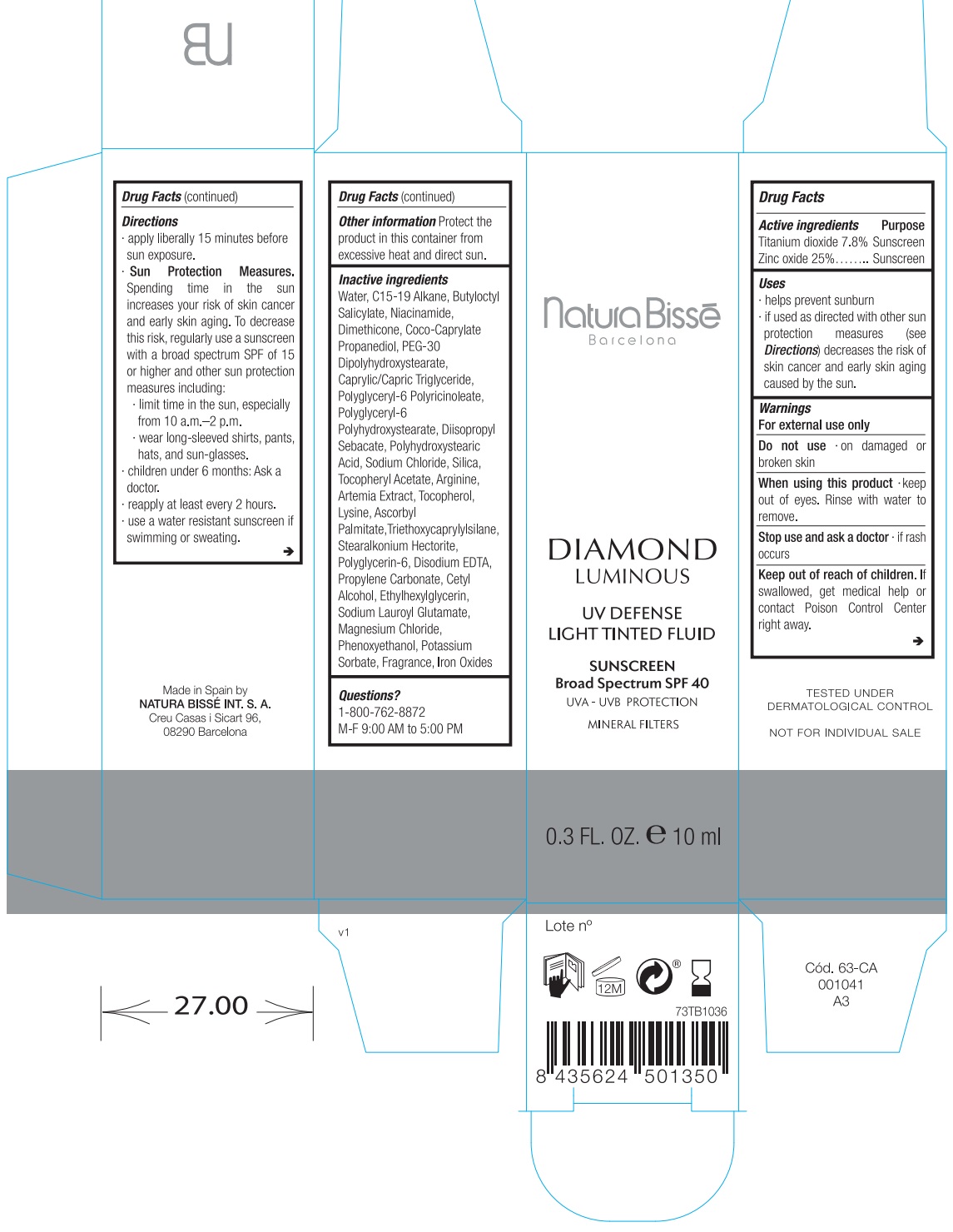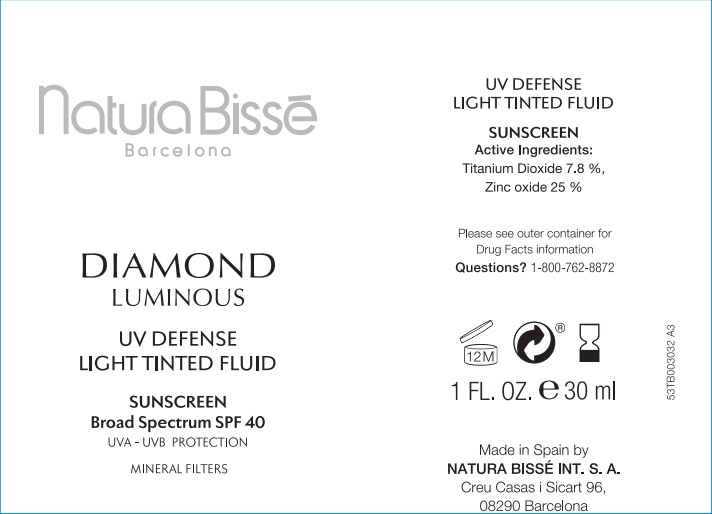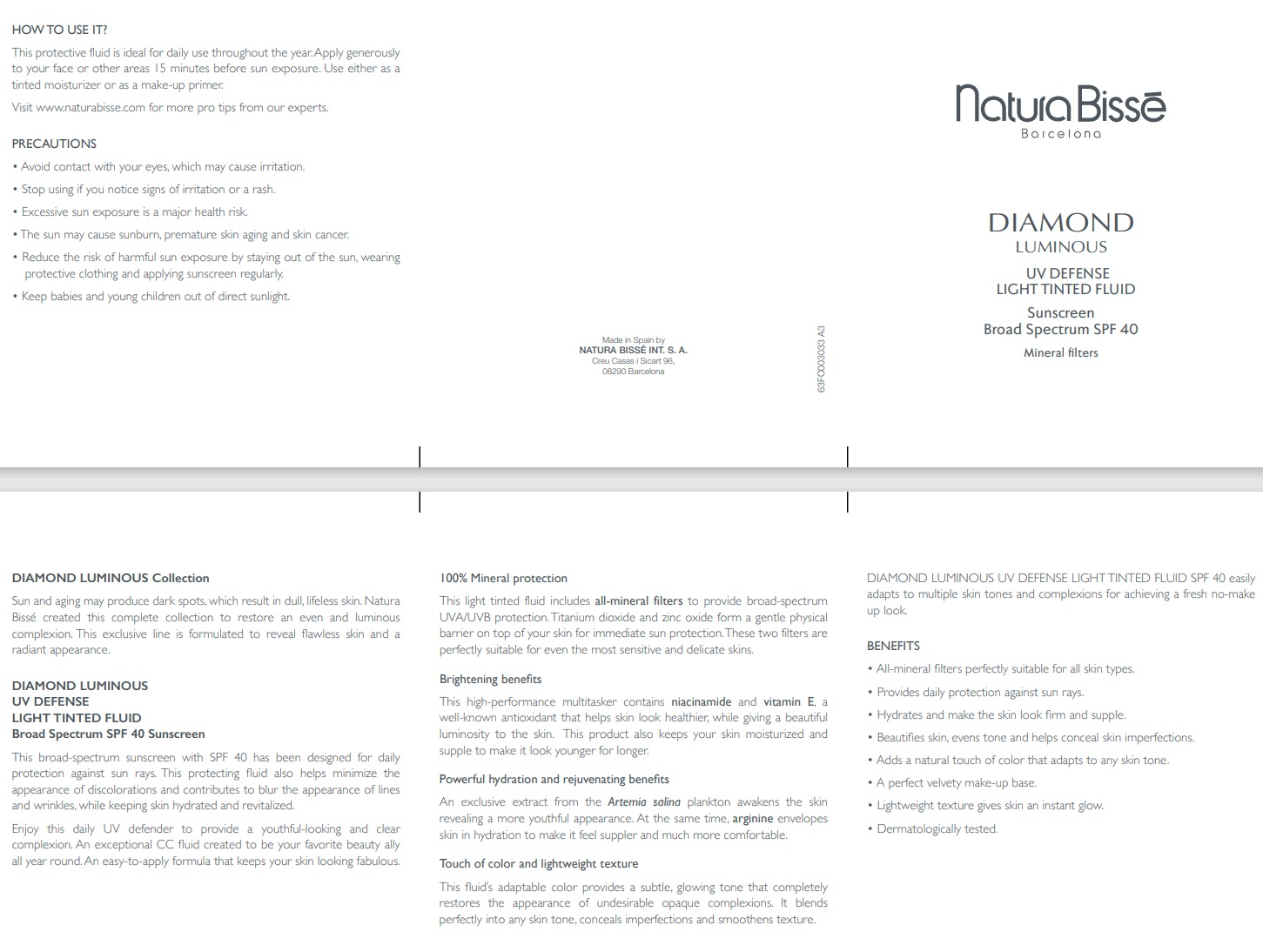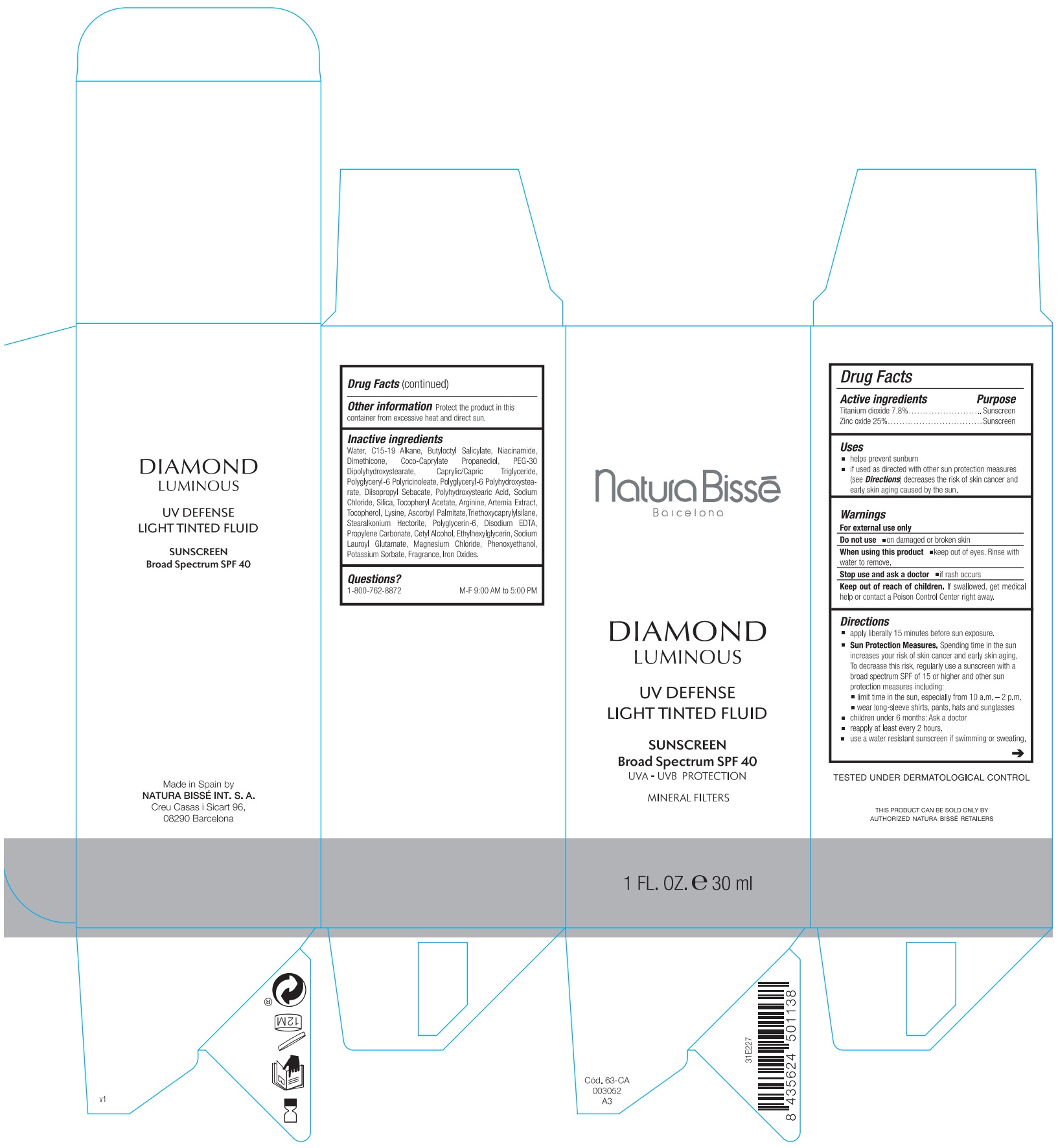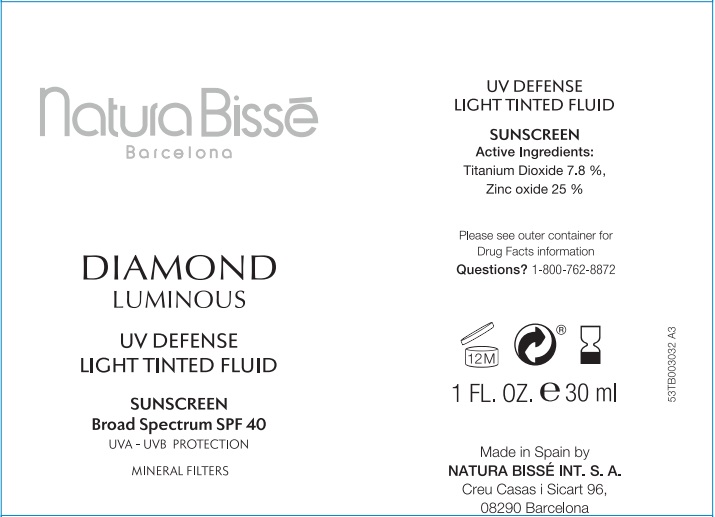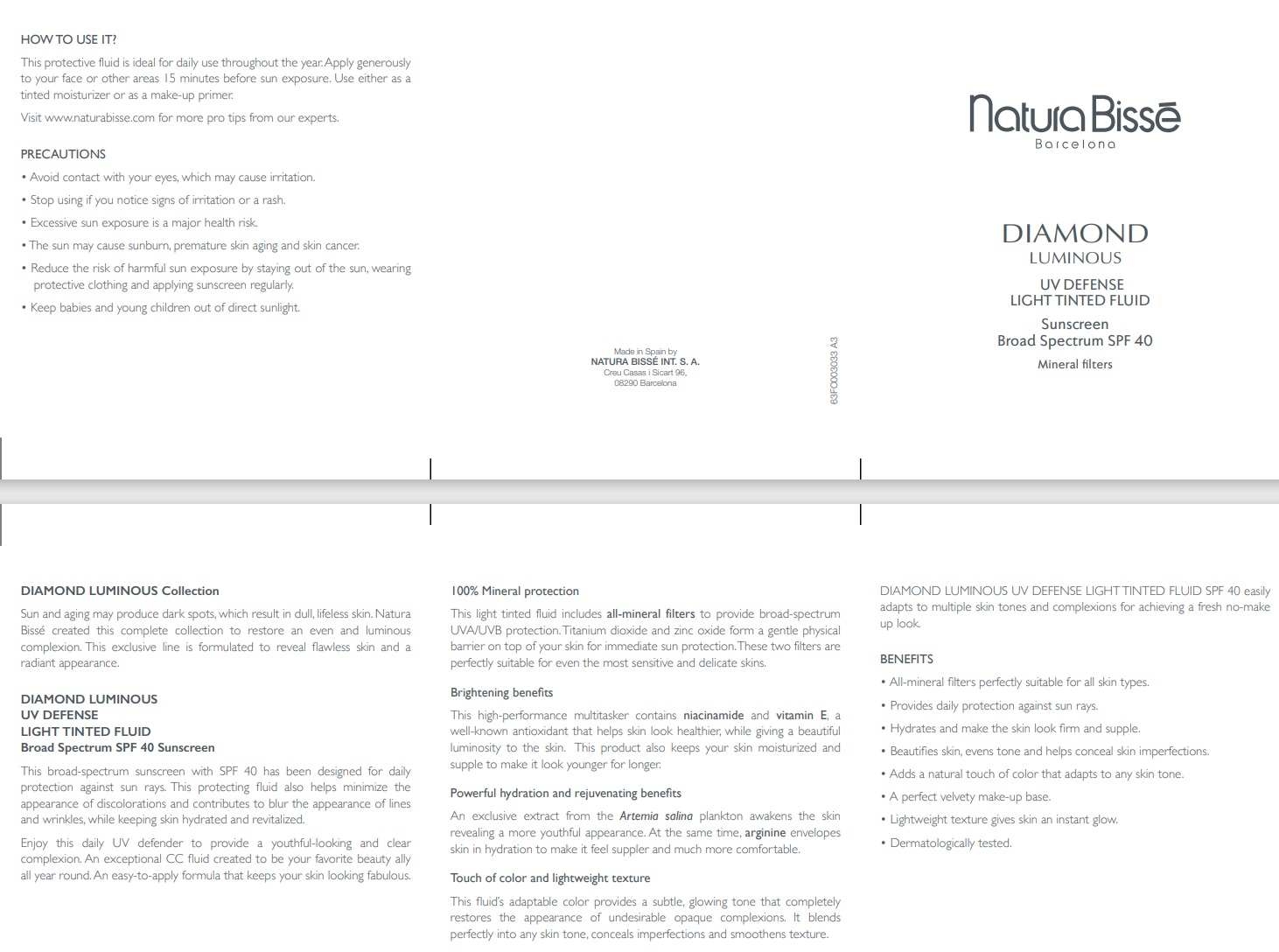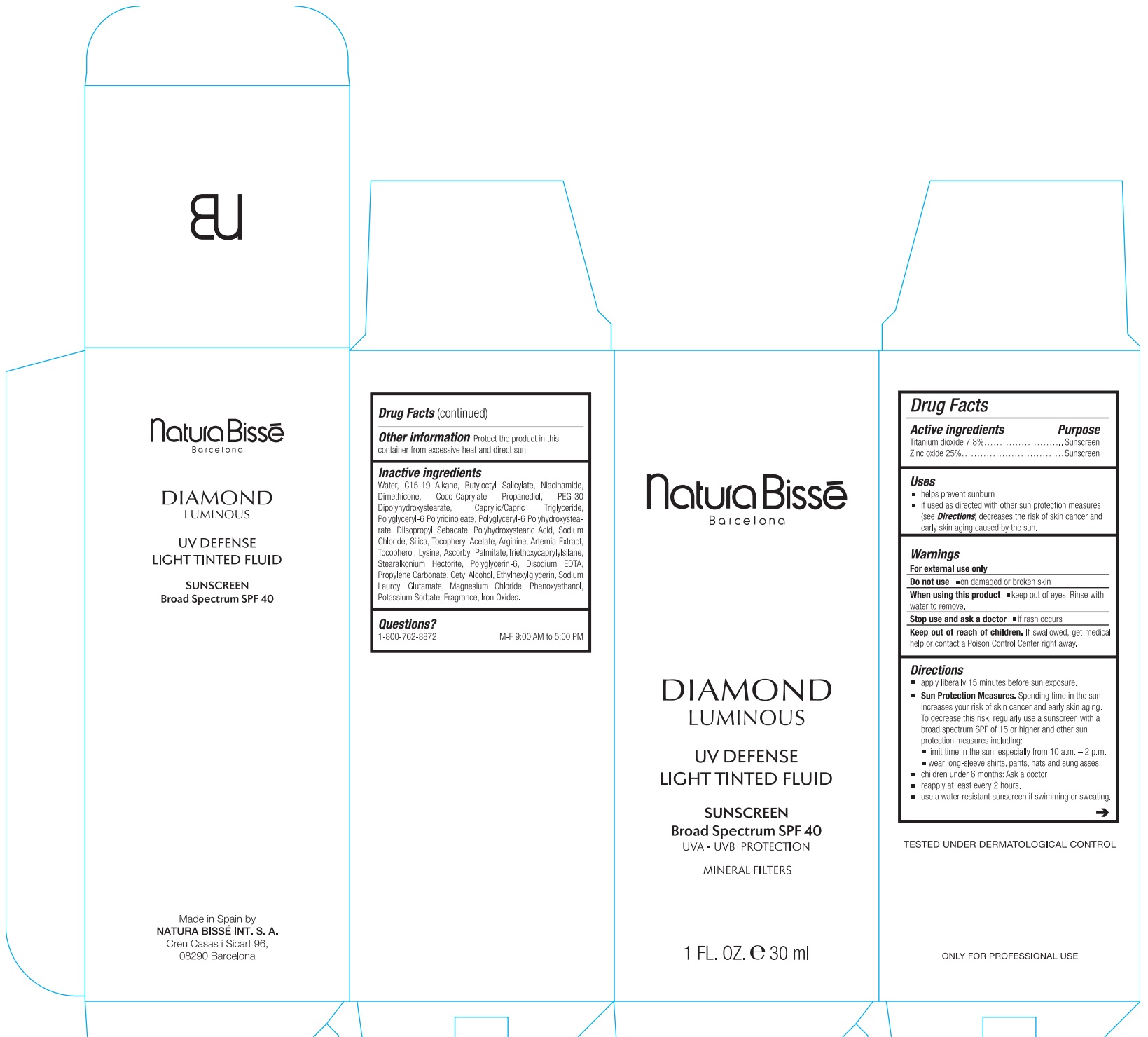 DRUG LABEL: Diamond Luminous UV Defense Light Tinted Fluid Sunscreen Broad Spectrum SPF 40
NDC: 63730-001 | Form: LOTION
Manufacturer: NATURA BISSE INTERNATIONAL SA
Category: otc | Type: HUMAN OTC DRUG LABEL
Date: 20231026

ACTIVE INGREDIENTS: TITANIUM DIOXIDE 78 mg/1 mL; ZINC OXIDE 250 mg/1 mL
INACTIVE INGREDIENTS: WATER; C15-19 ALKANE; BUTYLOCTYL SALICYLATE; NIACINAMIDE; DIMETHICONE; COCO-CAPRYLATE; PROPANEDIOL; PEG-30 DIPOLYHYDROXYSTEARATE; MEDIUM-CHAIN TRIGLYCERIDES; DIISOPROPYL SEBACATE; POLYGLYCERYL-6 POLYRICINOLEATE; SODIUM CHLORIDE; SILICON DIOXIDE; .ALPHA.-TOCOPHEROL ACETATE; ARGININE; TOCOPHEROL; LYSINE; ASCORBYL PALMITATE; TRIETHOXYCAPRYLYLSILANE; STEARALKONIUM HECTORITE; POLYGLYCERIN-6; EDETATE DISODIUM ANHYDROUS; PROPYLENE CARBONATE; CETYL ALCOHOL; ETHYLHEXYLGLYCERIN; SODIUM LAUROYL GLUTAMATE; MAGNESIUM CHLORIDE; PHENOXYETHANOL; POTASSIUM SORBATE; FERRIC OXIDE RED

Diamond Luminous UV Defense Light Tinted Fluid Sunscreen Broad Spectrum SPF 40

Active ingredients

Titanium dioxide 7.8%

Zinc oxide 25%

Purpose

Sunscreen

Uses

- helps prevent sunburn.
- If used as directed with other sun protection measures (see) decreases the risk of skin cancer and early skin aging caused by the sun. Directions

Warnings

For external use only

Do not use

on damaged or broken skin

When using this product

keep out of eyes. Rinse with water to remove.

Stop use and ask a doctor

if rash occurs

Keep out of reach of children.

If swallowed, get medical help or contact Poison Control Center right away.

Directions

apply liberally 15 minutes before sun exposure.

Spending time in the sun increases your risk of skin cancer and early skin aging. To decrease this risk, regularly use a sunscreen with a broad spectrum SPF of 15 or higher and other sun protection measures including: Sun Protection Measures.

- limit time in the sun, especially from 10 a.m.–2 p.m.
- wear long-sleeved shirts, pants, hats, and sunglasses.
- children under 6 months: Ask a doctor
- reapply at least every 2 hours.
- use a water resistant sunscreen if swimming or sweating.

RECENT MAJOR CHANGES

Directions have changed from:

apply liberally 15 minutes before sun exposure.

reapply:

Spending time in the sun increases your risk of skin cancer and early skin aging. To decrease this risk, regularly use a sunscreen with a broad spectrum SPF of 15 or higher and other sun protection measures including: Sun Protection Measures.

To:

apply liberally 15 minutes before sun exposure.

Sun Protection Measures. Spending time in the sun increases your risk of skin cancer and early skin aging. To decrease this risk, regularly use a sunscreen with a broad spectrum SPF of 15 or higher and other sun protection measures including:

- after 40 minutes of swimming or sweating
- Immediately after tower drying
- at least every 2 hours.

- limit time in the sun, especially from 10 a.m. – 2 p.m.
- wear long-sleeve shirts, pants, hats and sunglasses
- children under 6 months: Ask a doctor

- limit time in the sun, especially from 10 a.m.–2 p.m.
- wear long-sleeved shirts, pants, hats, and sunglasses.
- children under 6 months: Ask a doctor
- reapply at least every 2 hours.
- use a water resistant sunscreen if swimming or sweating.

Other information

Protect the product in this container from excessive heat and direct sun.

Inactive ingredients

Water, C15-19 Alkane, Butyloctyl Salicylate, Niacinamide, Dimethicone, Coco-Caprylate Propanediol, PEG-30 Dipolyhydroxystearate, Caprylic/Capric Triglyceride, Polyglyceryl-6 Polyricinoleate, Polyglyceryl-6 Polyhydroxystearate, Diisopropyl Sebacate, Polyhydroxystearic Acid, Sodium Chloride, Silica, Tocopheryl Acetate, Arginine, Artemia Extract, Tocopherol, Lysine, Ascorbyl Palmitate,Triethoxycaprylylsilane, Stearalkonium Hectorite, Polyglycerin-6, Disodium EDTA, Propylene Carbonate, Cetyl Alcohol, Ethylhexylglycerin, Sodium Lauroyl Glutamate, Magnesium Chloride, Phenoxyethanol, Potassium Sorbate, Fragrance, Iron Oxides.

Questions?

1-800-762-8872 M-F 9:00 AM to 5:00 PM